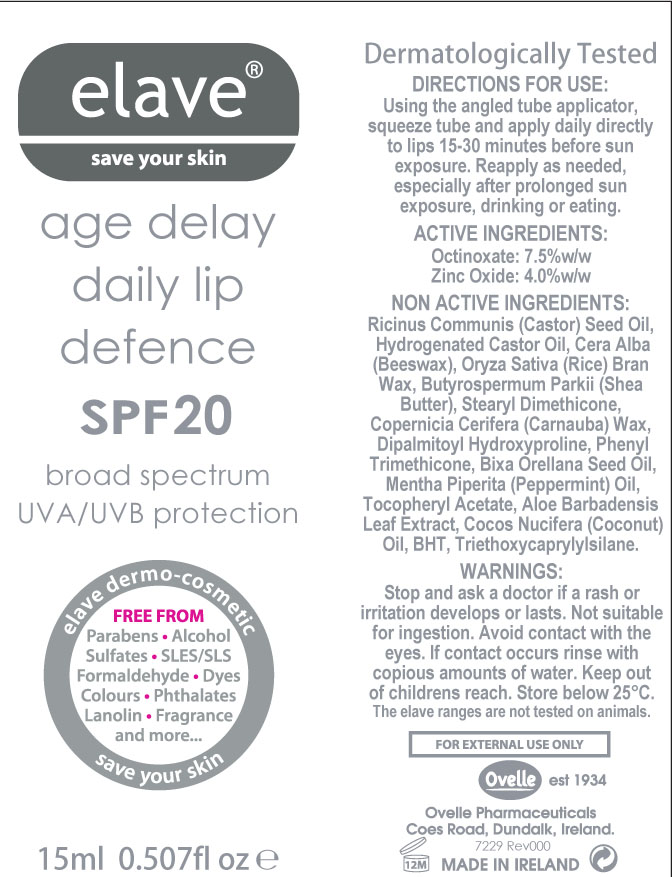 DRUG LABEL: elave Age Delay Daily Lip Defence
NDC: 46006-002 | Form: OINTMENT
Manufacturer: Ovelle Ltd
Category: otc | Type: HUMAN OTC DRUG LABEL
Date: 20111213

ACTIVE INGREDIENTS: Octinoxate 1.125 mL/15 mL; Zinc Oxide 0.6 mL/15 mL
INACTIVE INGREDIENTS: Castor Oil; Hydrogenated Castor Oil; Yellow Wax; Rice Bran; Shea Butter; Dimethicone; Carnauba Wax; Dipalmitoyl Hydroxyproline; Phenyl Trimethicone; Bixa Orellana Seed Oil; Peppermint Oil; Alpha-Tocopherol Acetate; Aloe Vera Leaf; Coconut Oil; Butylated Hydroxytoluene; Triethoxycaprylylsilane

DRUG FACTS

ACTIVE INGREDIENTS PURPOSE
Octinoxate 7.5%w/w Sunscreen
Zinc Oxide 4.0%w/w Sunscreen

USES

- helps protect against sunburn
- for lips that sunburn easily
- helps provide protection against UVA and UVB rays

WARNINGS

For external use only

Do not use on

- broken skin
- serious burns

When using this product

- keep out of the eyes. Rinse with water to remove
- not suitable for ingestion

Stop use and ask a doctor if

- rash or irritation develops and lasts

Keep out of reach of children
If swallowed get medical help or contact a Poison Control Center right away

DIRECTIONS

- apply to lips 15 - 20 minutes before sun exposure
- re-apply as needed, especially after prolonged sun exposure, drinking or eating

OTHER INFORMATION

- store below 25C, do not freeze
- not recommended for children under 6 months of age

INACTIVE INGREDIENTS

Ricinus Communis (Castor) Seed Oil, Hydrogenated Castor Oil, Cera Alba (Beeswax), Oryza Sativa (Rice) Bran Wax, Butyrospermum Parkii (Shea Butter), Stearyl Dimethicone, Copernicia Cerifera (Carnauba) Wax, Dipalmitoyl Hydroxyproline, Phenyl Trimethicone, Bixa Orellana Seed Oil, Mentha Piperita (Peppermint Oil), Tocopheryl Acetate, Aloe Barbadensis Leaf Extract, Cocos Nucifera (Coconut) Oil, BHT, Triethoxycaprylylsilane

QUESTIONS OR COMMENTS

Distributor: Ashette LLC, 27-28 Thomson Ave, Long Island City NY11101

www.ashette.com

Manufacturer: Ovelle Pharmaceuticals, Coes Road, Dundalk, Co Louth, Ireland

PACKAGE LABEL

age delay daily lip defence

SPF20

Sensitive Formula

Broad-Spectrum UVA/UVB Protection

Preservative Fee

Anti-oxidant Vitamin E

Soothing Aloe Vera Leaf Extract

Triple Firming Natural Lipoamino Acid

Refreshing Peppermint Oil

FREE FROM

Parabens, Alcohol, Sulfates, SLES/SLS, Formaldehyde, Dyes, Colours, Phthalates, Lanolin, Fragrance

PACKAGE LABEL

4600600201